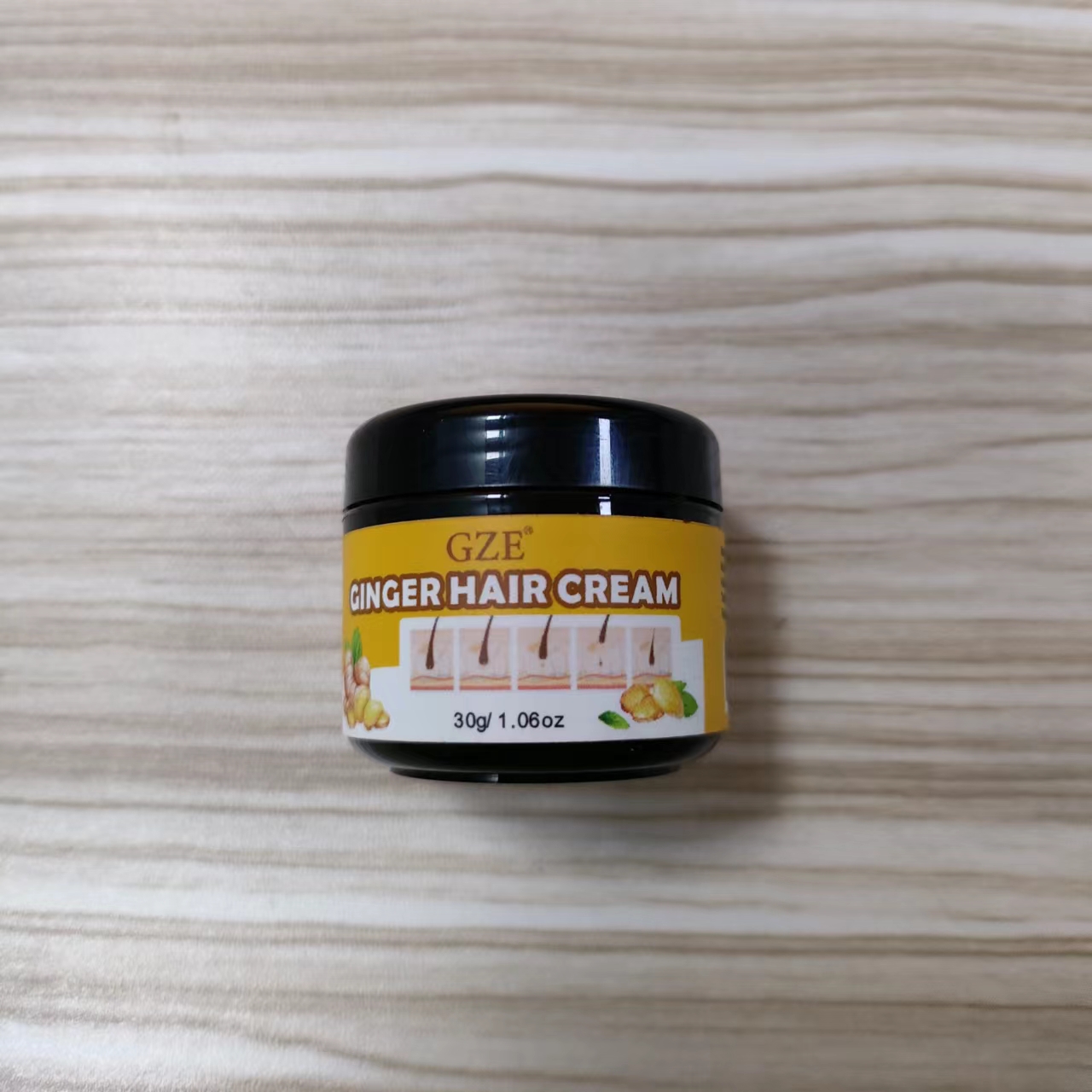 DRUG LABEL: GZE Ginger Hair Cream
NDC: 74458-115 | Form: CREAM
Manufacturer: Guangzhou Yilong Cosmetics Co., Ltd
Category: otc | Type: HUMAN OTC DRUG LABEL
Date: 20241107

ACTIVE INGREDIENTS: ZINGIBER OFFICINALE (GINGER) ROOT EXTRACT 46.4 g/100 g
INACTIVE INGREDIENTS: AQUA; ORBIGNYA OLEIFERA SEED OIL; PARFUMIDINE; CARBOMER; GLYCERIN; MALTODEXTRIN/VP COPOLYMER (1000 MPA.S); XANTHAN GUM; ACRYLATES CROSSPOLYMER-4; COCOS NUCIFERA (COCONUT) OIL; ALOE BARBADENSIS LEAF JUICE; PECTIN

GZE Ginger Hair Cream

ACTIVE INGREDIENT

Zingiber Officinale (Ginger) Extract

INACTIVE INGREDIENT

Aqua

Glycerin

Aloe Barbadensis Leaf Juice

Acrylates Copolymer

Cocos Nucifera (Coconut) Oil

Orbignya Oleifera Seed Oil

Maltodextrin/Vp Copolymer

Pectin

Parfum

Carbomer

Xanthan Gum

PURPOSE

Hair growth

INDICATIONS AND USAGE

Smooth onto damp hair, section by section，beginning at the ends and working towards the root, do not rinse.

WARNINGS

For external use only.

Stop use and ask a doctor if rash occurs.

Do not use on damaged or broken skin.

When using this product keep out of eyes. Rinse with water to remove.

Keep out of reach of children. If swallowed, get medical help or contact a Poison Control Center right away.

DOSAGE AND ADMINISTRATION

Smooth onto damp hair, section by section，beginning at the ends and working towards the root, do not rinse.